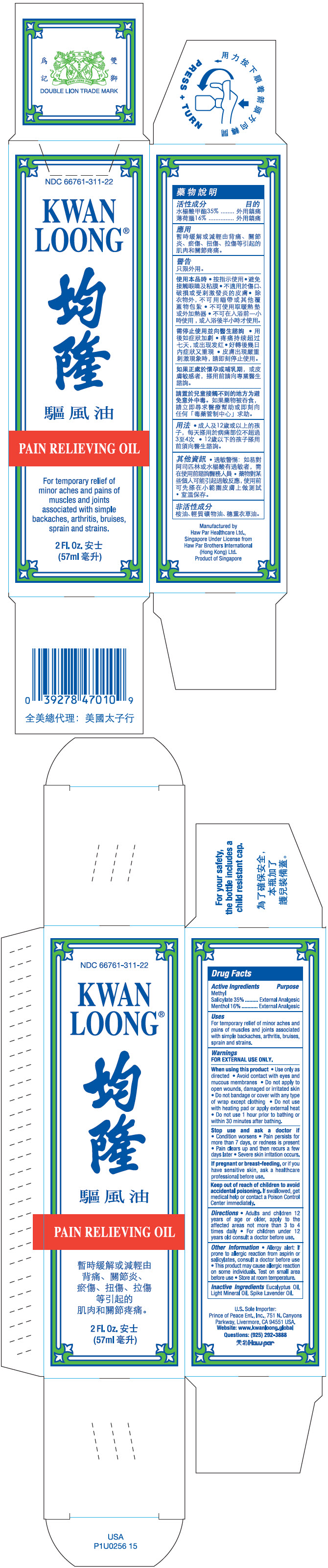 DRUG LABEL: Kwan Loong
NDC: 66761-311 | Form: OIL
Manufacturer: Haw Par Healthcare Ltd.
Category: otc | Type: HUMAN OTC DRUG LABEL
Date: 20251217

ACTIVE INGREDIENTS: Methyl salicylate 350 mg/1 mL; Menthol, Unspecified Form 160 mg/1 mL
INACTIVE INGREDIENTS: Eucalyptus Oil; Spike Lavender Oil; Light Mineral Oil

Kwan Loong®

Drug Facts

ACTIVE INGREDIENT

Active Ingredients | Purpose
Methyl Salicylate 35% | External Analgesic
Menthol 16% | External Analgesic

Uses

For temporary relief of minor aches and pains of muscles and joints associated with simple backaches, arthritis, bruises, sprain and strains.

Warnings

FOR EXTERNAL USE ONLY.

When using this product

- Use only as directed
- Avoid contact with eyes and mucous membranes
- Do not apply to open wounds, damaged or irritated skin
- Do not bandage or cover with any type of wrap except clothing
- Do not use with heating pad or apply external heat
- Do not use 1 hour prior to bathing or within 30 minutes after bathing.

Stop use and ask a doctor if

- Condition worsens
- Pain persists for more than 7 days, or redness is present
- Pain clears up and then recurs a few days later
- Severe skin irritation occurs.

PREGNANCY OR BREAST FEEDING

If pregnant or breast-feeding, or if you have sensitive skin, ask a healthcare professional before use.

Keep out of reach of children to avoid accidental poisoning. If swallowed, get medical help or contact a Poison Control Center immediately.

Directions

- Adults and children 12 years of age or older, apply to the affected areas not more than 3 to 4 times daily
- For children under 12 years old consult a doctor before use.

Other Information

- Allergy alert: If prone to allergic reaction from aspirin or salicylates, consult a doctor before use
- This product may cause allergic reaction on some individuals. Test on small area before use.
- Store at room temperature.

Inactive Ingredients

Eucalyptus Oil, Light Mineral Oil, Spike Lavender Oil.

Questions

(925) 292-3888

Manufactured by
Haw Par Healthcare Ltd.,
Singapore

PRINCIPAL DISPLAY PANEL - 57 ml Bottle Box

NDC 66761-311-22

KWAN
LOONG®

PAIN RELIEVING OIL

For temporary relief of
minor aches and pains of
muscles and joints
associated with simple
backaches, arthritis, bruises,
sprain and strains.

2 Fl. Oz.
(57ml)